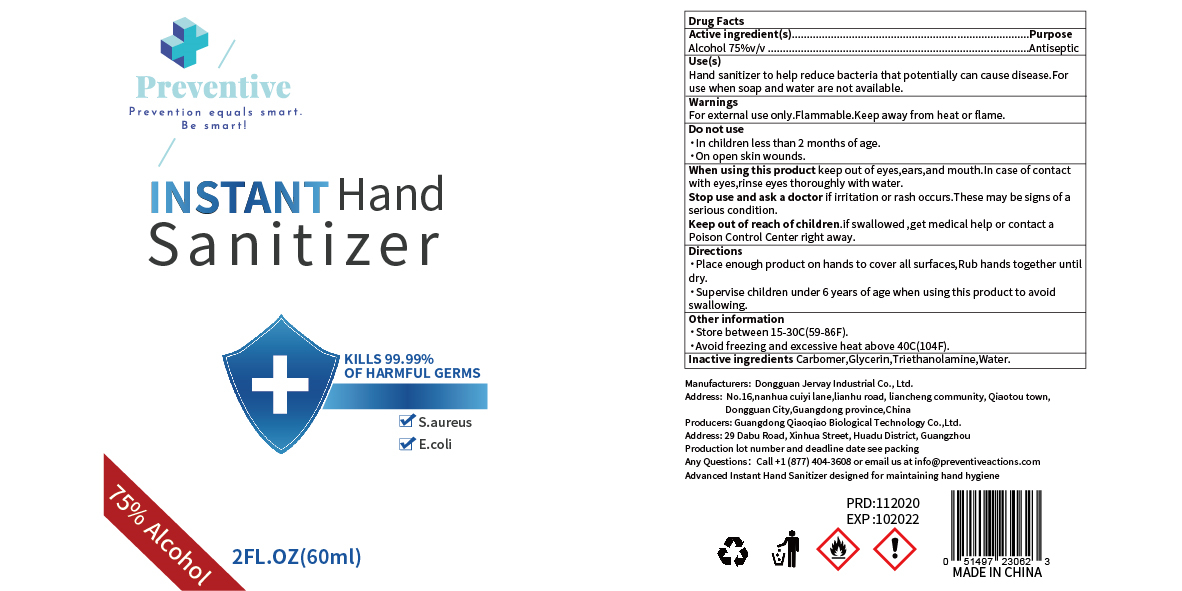 DRUG LABEL: Hand sanitizer
NDC: 41876-008 | Form: LIQUID
Manufacturer: Dongguan Jervay Industrial Co.,LTD
Category: otc | Type: HUMAN OTC DRUG LABEL
Date: 20220530

ACTIVE INGREDIENTS: ALCOHOL 45 mL/60 mL
INACTIVE INGREDIENTS: GLYCERIN; TROLAMINE; WATER; CARBOMER HOMOPOLYMER, UNSPECIFIED TYPE

DOSAGE AND ADMINISTRATION

Store between 15-30°C(59-86°F).Avoid freezing and excessive heat above 40°C(104°F).

INACTIVE INGREDIENT

Carbomer

Glycerol

Triethanolamine

Water

INDICATIONS AND USAGE

Place enough product on hands to cover all surfaces,Rub hands together until dry.

ACTIVE INGREDIENT

Alcohol

DO NOT USE

1.ln children less than 2 months of age.

2.On open skin wounds.

keep out of reach of children

PURPOSE

Disinfection
Sterilization

WARNINGS

For external use only.Flammable.Keep away from heat or flame.